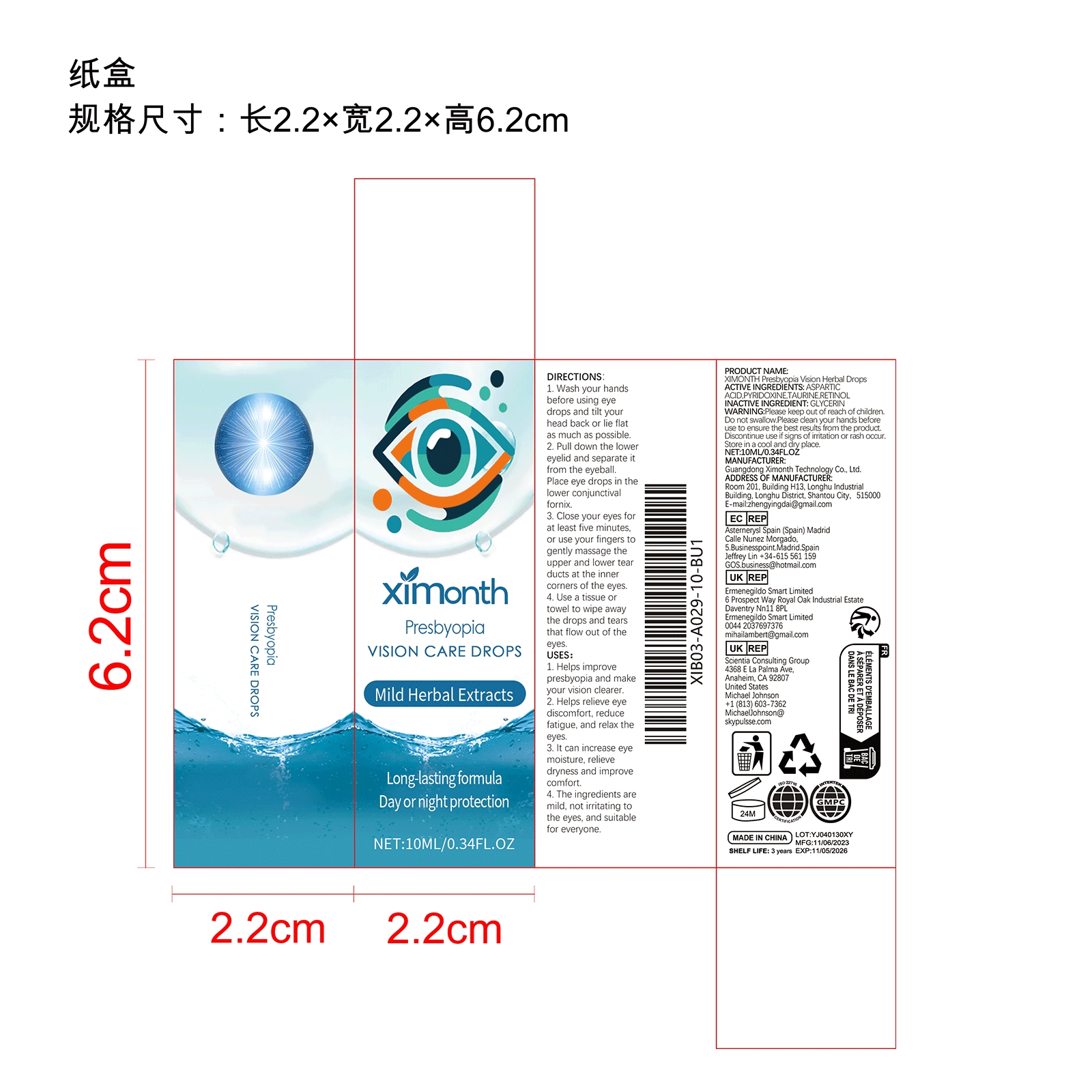 DRUG LABEL: XIMONTH Presbyopia Vision Herbal Drops
NDC: 84660-054 | Form: LIQUID
Manufacturer: Guangdong Ximonth Technology Co., Ltd.
Category: otc | Type: HUMAN OTC DRUG LABEL
Date: 20241101

ACTIVE INGREDIENTS: PYRIDOXINE 1 mg/10 mg; TAURINE 1.5 mg/10 mg; RETINOL 1.5 mg/10 mg; ASPARTIC ACID 3 mg/10 mg
INACTIVE INGREDIENTS: GLYCERIN 3 mg/10 mg

ACTIVE INGREDIENTS

ASPARTIC ACID,PYRIDOXINE,TAURINE,RETINOL

PURPOSE

1. Helps improve presbyopia and make your vision clearer.

2. Helps relieve eye discomfort, reduce fatigue, and relax the eyes.

3. It can increase eye moisture, relieve dryness and improve comfort.

4. The ingredients are mild, not irritating to the eyes, and suitable for everyone.

USES

1. Wash your hands before using eye drops and tilt your head back or lie flat as much as possible.

2. Pull down the lower eyelid and separate it from the eyeball Place eye drops in the lower conjunctival fornix.

3. Close your eyes for at least five minutes, or use your fingers to gently massage the upper and lower tear ducts at the inner corners of the eyes.

4. Use a tissue or towel to wipe away the drops and tears that flow out of the eyes.

WARNING

Please keep out of reach of children.Do not swallow.Please clean your hands before use to ensure the best results from the product. Discontinue use if signs of irritation or rash occur. Store in a cool and dry place.

STOP USE

Discontinue use if signs of irritation or rash occur.

DO NOT USE

Discontinue use if signs of irritation or rash occur.

KEEP OUT OF REACH OF CHILDREN

Please keep out of reach of children. Do not swallow.

STORAGE AND HANDLING

Store in a cool and dry place.

INACTIVE INGREDIENT

GLYCERIN